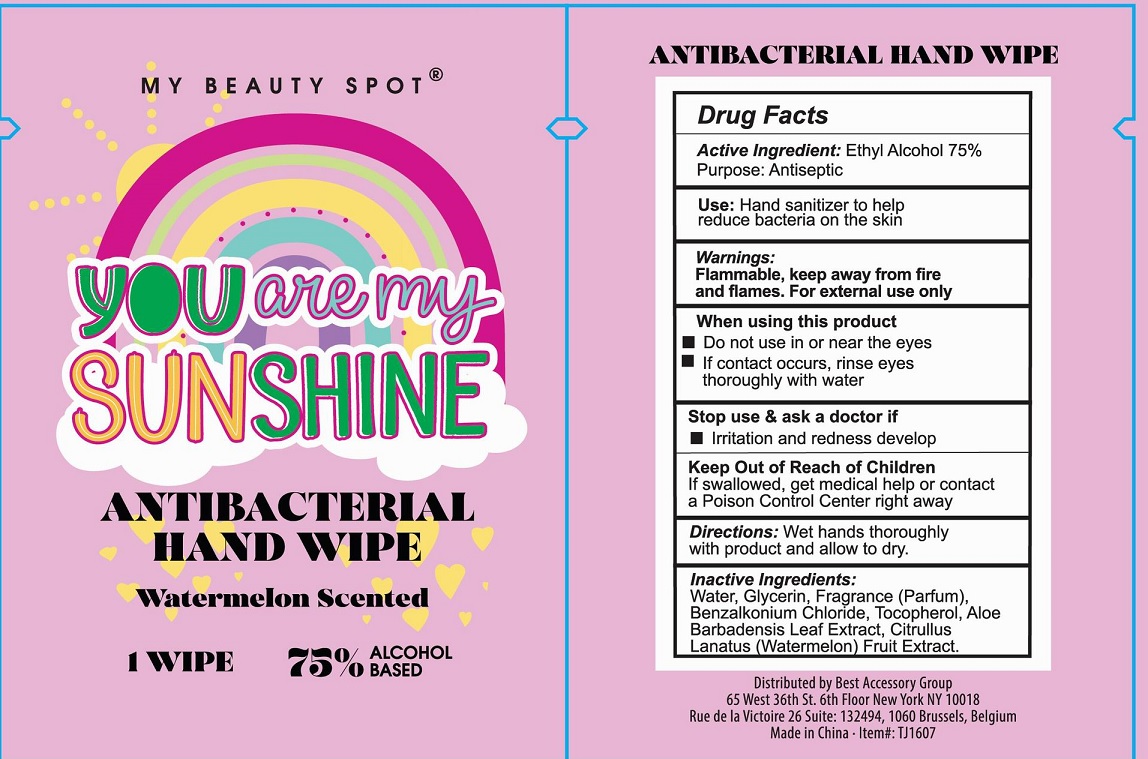 DRUG LABEL: You Are My Sunshine Antibacterial Hand Wipes Watermelon Scented
NDC: 42129-110 | Form: CLOTH
Manufacturer: Fustin(Xiamen) Commodity Co., ltd
Category: otc | Type: HUMAN OTC DRUG LABEL
Date: 20201019

ACTIVE INGREDIENTS: ALCOHOL 75 1/100 1
INACTIVE INGREDIENTS: WATER; GLYCERIN; BENZALKONIUM CHLORIDE; TOCOPHEROL

Alcohol wipes

Active Ingredient

Ethyl Alcohol 75%

Purpose

Antiseptic

Warnings

For external use only.
Flammable. Keep away from fire or flame.
When using this product Do not use in or near the eyes, if contact occurs, rinse eyes thoroughly with water.

Stop use and ask a doctor if irritation and redness develop.

INDICATIONS AND USAGE

Hand sanitizer to help reduce bacteria on the skin.

Keep out of reach of children. If swallowed, get medical help or contact a Poison Control Center right away.

Directions

Wet hands htoroughly with product and allow to dry.

Inactive ingredients

Water, Glycerin, Fragrance (Parfum), Benzalkonium Chloride, Tocopherol, Aloe Barbadensis Leaf Extract. Citrullus Lanatus (Watermelon) Fruit Extract.